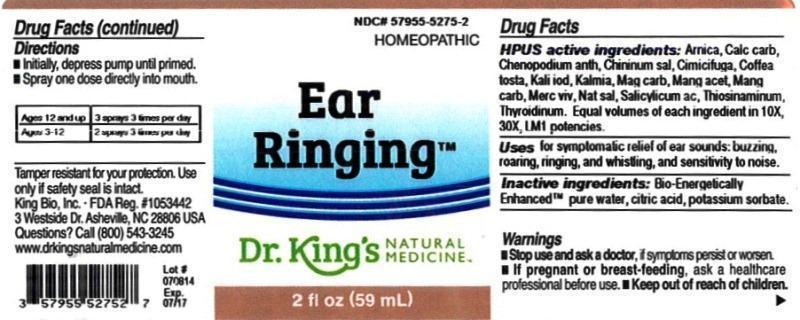 DRUG LABEL: Ear Ringing
NDC: 57955-5275 | Form: LIQUID
Manufacturer: King Bio Inc.
Category: homeopathic | Type: HUMAN OTC DRUG LABEL
Date: 20140806

ACTIVE INGREDIENTS: ARNICA MONTANA 10 [hp_X]/59 mL; OYSTER SHELL CALCIUM CARBONATE, CRUDE 10 [hp_X]/59 mL; DYSPHANIA AMBROSIOIDES 10 [hp_X]/59 mL; QUININE SALICYLATE 10 [hp_X]/59 mL; BLACK COHOSH 10 [hp_X]/59 mL; COFFEA ARABICA SEED, ROASTED 10 [hp_X]/59 mL; POTASSIUM IODIDE 10 [hp_X]/59 mL; KALMIA LATIFOLIA LEAF 10 [hp_X]/59 mL; MAGNESIUM CARBONATE 10 [hp_X]/59 mL; MANGANESE ACETATE TETRAHYDRATE 10 [hp_X]/59 mL; MANGANESE CARBONATE 10 [hp_X]/59 mL; MERCURY 10 [hp_X]/59 mL; SODIUM SALICYLATE 10 [hp_X]/59 mL; SALICYLIC ACID 10 [hp_X]/59 mL; ALLYLTHIOUREA 10 [hp_X]/59 mL; THYROID, UNSPECIFIED 10 [hp_X]/59 mL
INACTIVE INGREDIENTS: WATER; CITRIC ACID MONOHYDRATE; POTASSIUM SORBATE

Ear Ringing™

Drug Facts

___________________________________________________________________________________________________________________

HPUS active ingredients: Arnica montana, Calcarea carbonica, Chenopodium anthelminticum, Chininum salicylicum, Cimicifuga racemosa, Coffea tosta, Kali iodatum, Kalmia latifolia, Magnesia carbonica, Manganum aceticum, Manganum carbonicum, Mercurius vivus, Natrum salicylicum, Salicylicum acidum, Thiosinaminum, Thyroidinum. Equal volumes of each ingredient in 10X, 30X, LM1 potencies.

INDICATIONS AND USAGE

Uses for symptomalic relief of ear sounds: buzzing, roaring, ringing, and whistling, and sensitivity to noise.

INACTIVE INGREDIENT

Inactive ingredients: Bio-Energetically Enhanced™ pure water, citric acid, potassium sorbate.

Warnings

- Stop use and ask your doctor if symptoms persist or worsen.
- If pregnant or breast-feeding, ask a healthcare professional before use.

- Keep out of reach of children.

Directions

- Initially, depress pump until primed.
- Spray one dose directly into mouth.

Ages 12 and up: 3 sprays 3 times per day

Ages 2-12: 2 sprays 3 times per day

OTHER SAFETY INFORMATION

Tamper resistant for your protection. Use only if safety seal is intact.

PURPOSE

Uses for symptomalic relief of ear sounds: buzzing, roaring, ringing, and whistling, and sensitivity to noise.